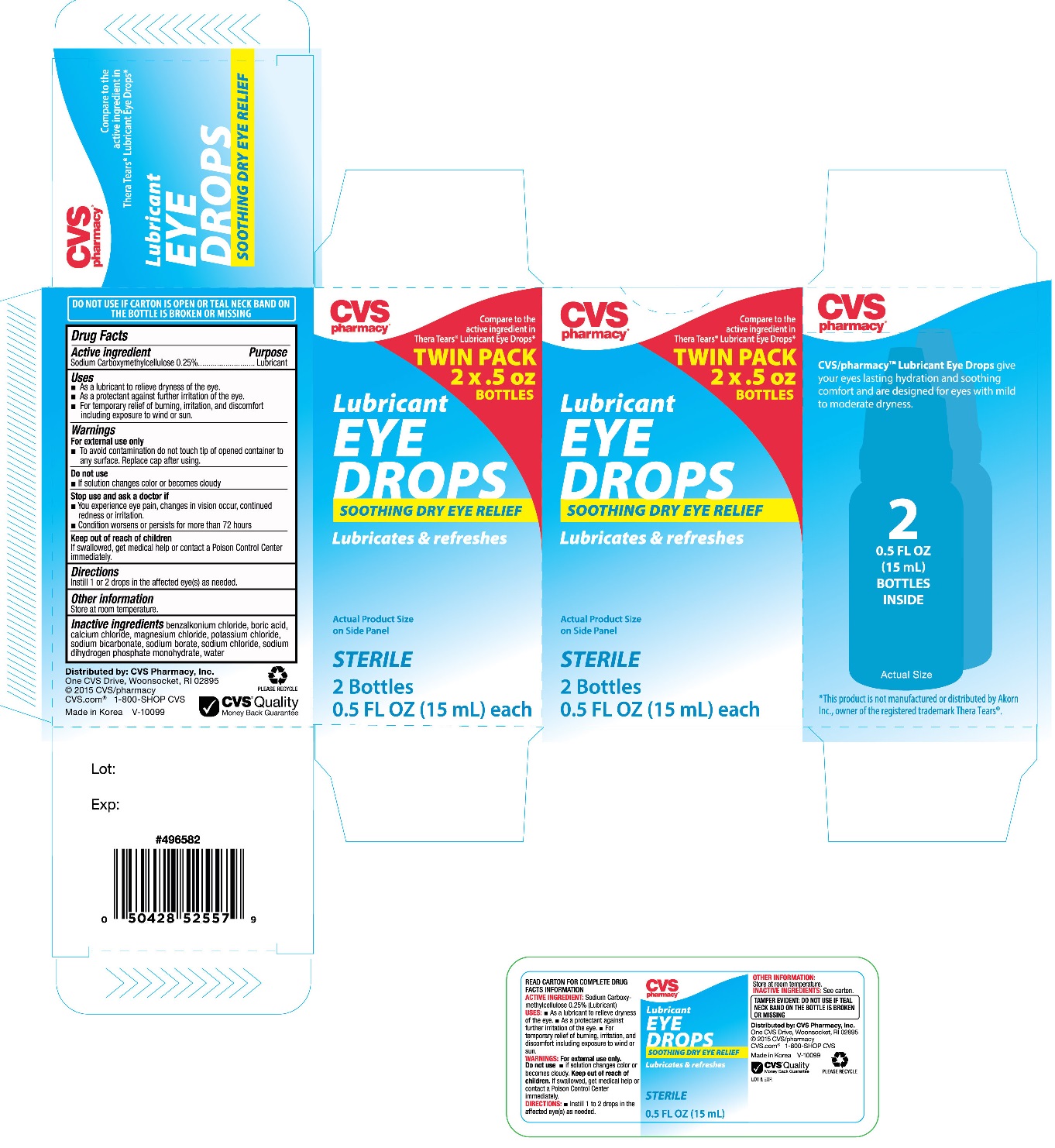 DRUG LABEL: CVS Lubricant Eye
NDC: 59779-755 | Form: SOLUTION/ DROPS
Manufacturer: CVS Pharmacy
Category: otc | Type: HUMAN OTC DRUG LABEL
Date: 20171127

ACTIVE INGREDIENTS: CARBOXYMETHYLCELLULOSE SODIUM 2.5 mg/1 mL
INACTIVE INGREDIENTS: BENZALKONIUM CHLORIDE; BORIC ACID; CALCIUM CHLORIDE; MAGNESIUM CHLORIDE; POTASSIUM CHLORIDE; SODIUM BICARBONATE; SODIUM BORATE; SODIUM CHLORIDE; SODIUM PHOSPHATE, MONOBASIC, DIHYDRATE; WATER

CVS Lubricant Eye Drops Twin Pack (NB Thera Tears)

Active ingredient Purpose

Sodium Carboxymethylcellulose 0.25%............................Lubricant

Uses

- As a lubricant to relieve dryness of the eye
- As a protectant against further irritation of the eye
- For temporary relief of burning, irritation, and discomfort including exposure to wind or sun

Warnings

For external use only.

- To avoid contamination do not touch tip of opened container to any surface. Replace cap after using.

Do not use

- if solution changes color or becomes cloudy

Stop use and ask a doctor if

- You experience eye pain, changes in vision occur, continued redness or irritation
- Condition worsens or persists for more than 72 hours

Keep out of reach of children

If swallowed, get medical help or contact a Poison Control Center immediately

Keep out of reach of children

If swallowed, get medical help or contact a Poison Control Center immediately

Directions

Instill 1 or 2 drops in the affected eye(s) as needed

Other information

Store at room temperature

Inactive ingredients

benzalkonium chloride, boric acid, calcium chloride, magnesium chloride, potassium chloride, sodium bicarbonate, sodium borate, sodium chloride, sodium dihydrogen phosphate monohydrate, water

DOSAGE AND ADMINISTRATION

Distributed by:

CVS Pharmacy, Inc.

One CVS Drive

Woonsocket, RI 02895

Made in Korea